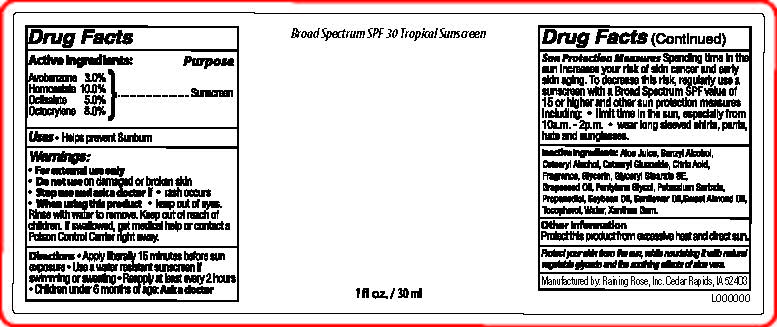 DRUG LABEL: Broad Spectrum SPF 30 Tropical Sunscreen
NDC: 65692-0577 | Form: LOTION
Manufacturer: Raining Rose, Inc
Category: otc | Type: HUMAN OTC DRUG LABEL
Date: 20240520

ACTIVE INGREDIENTS: OCTISALATE 1.5 g/30 mL; AVOBENZONE 0.9 g/30 mL; OCTOCRYLENE 2.4 g/30 mL; HOMOSALATE 3 g/30 mL
INACTIVE INGREDIENTS: GLYCERIN; SOYBEAN OIL; ALOE VERA LEAF; POTASSIUM SORBATE; TOCOPHEROL; WATER; CETEARYL GLUCOSIDE; CETOSTEARYL ALCOHOL; GRAPE SEED OIL; SUNFLOWER OIL; XANTHAN GUM; PENTYLENE GLYCOL; ALMOND OIL; ANHYDROUS CITRIC ACID; BENZYL ALCOHOL; GLYCERYL STEARATE SE; PROPANEDIOL

Active Ingredients:

Avobenzone 3%

Homosalate 10%

Octisalate 5%

Octocrylene 8%

PURPOSE

Sunscreen

INDICATIONS AND USAGE

Helps prevent sunburn

WARNINGS

For external use only. Do not use on damaged or broken skin. Stop use and ask a doctor if rash occurs. When using this product keep out of eyes. Rinse with water to remove.

Keep out of reach of children. If swallowed, get medical help or contact a poison control center right away.

DOSAGE AND ADMINISTRATION

Apply liberally 15 minutes before sun exposure
Reapply after 80 minutes of swimming or sweating.
Reapply immediately after towel drying.
Reapply at least every 2 hours
Children under 6 months of age: Ask a doctor

Sun Protection Measures Spending time in the sun increases your risk of skin cancer and early skin aging. To decrease this risk, regularly use a sunscreen with a Broad Spectrum SPF value of 15 or higher and other sunprotection measures including:

limit time in the sun, especially from 10a.m.-2p.m.
wear long sleeved shirts, pants, hats and sunglasses.

OTHER SAFETY INFORMATION

Protect this product from excessive heat and direct sun.

INACTIVE INGREDIENT

Aloe Juice, Benzyl Alcohol, Cetearyl Alcohol, Cetearyl Glucoside, Citric Acid, Fragrance, Glycerin, Glyceryl Stearate SE, Grapeseed Oil, Pentylene Glycol, Potassium Sorbate, Propanediol, Soybean Oil, Sunflower Oil, Sweet Almond Oil, Tocopherol, Water, Xanthan Gum.